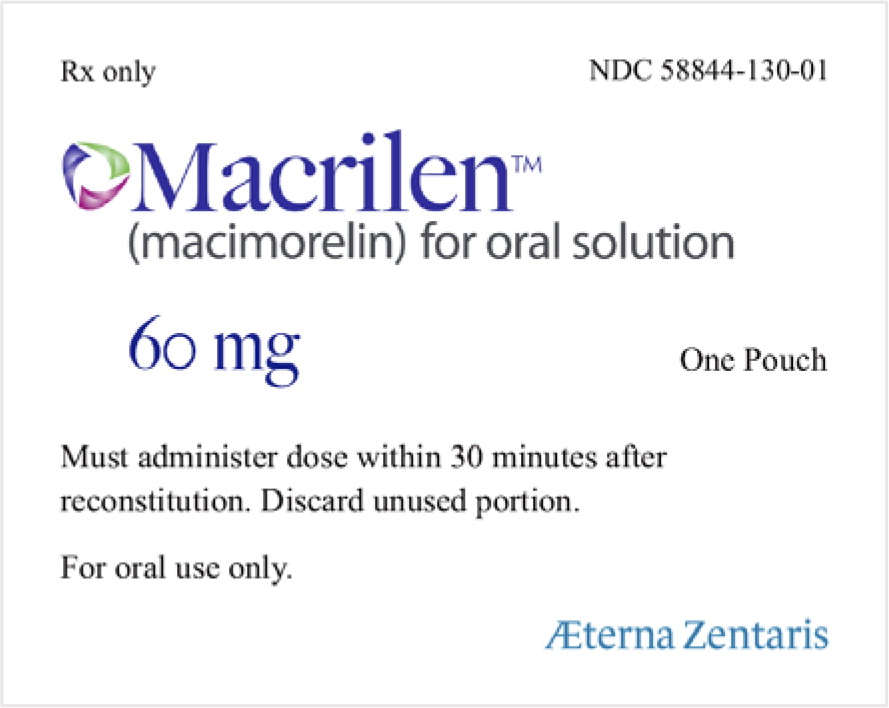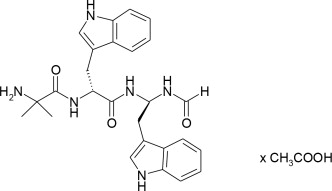 DRUG LABEL: Macrilen
NDC: 58844-130 | Form: GRANULE, FOR SOLUTION
Manufacturer: Aeterna Zentaris GmbH
Category: prescription | Type: HUMAN PRESCRIPTION DRUG LABEL
Date: 20260218

ACTIVE INGREDIENTS: MACIMORELIN 60 mg/1817 mg
INACTIVE INGREDIENTS: CROSPOVIDONE, UNSPECIFIED; SILICON DIOXIDE; SODIUM STEARYL FUMARATE; SACCHARIN SODIUM; LACTOSE MONOHYDRATE

HIGHLIGHTS OF PRESCRIBING INFORMATION

These highlights do not include all the information needed to use MACRILEN safely and effectively. See full prescribing information for MACRILEN.
MACRILEN (macimorelin) for oral solution
Initial U.S. Approval: 2017

1 INDICATIONS AND USAGE

MACRILEN is a growth hormone (GH) secretagogue receptor agonist indicated for the diagnosis of adult growth hormone deficiency (1).

Limitations of Use:

The safety and diagnostic performance has not been established for subjects with BMI > 40kg/m^2(1).

2 DOSAGE AND ADMINISTRATION

- Recommended dose is 0.5 mg/kg as a single oral dose, after fasting for at least 8 hours (2.1).
- See Full Prescribing Information for important preparation and administration instructions (2.3).
- Discontinue therapy with strong CYP3A4 inducers, growth hormones and drugs that affect GH release for an adequate length of time before administering MACRILEN (2.2).
- Adequately replace other hormone deficiencies before administering MACRILEN (2.2).

3 DOSAGE FORMS AND STRENGTHS

For oral solution: 60 mg (3)

4 CONTRAINDICATIONS

None (4)

5 WARNINGS AND PRECAUTIONS

- QT Prolongation:QT prolongation can lead to development of torsade de pointes-type ventricular tachycardia. Avoid the concomitant use of MACRILEN with drugs that are known to prolong QT interval (5.1, 7.1).
- Potential for False Positive Test Results with Use of Strong CYP3A4 Inducers:Discontinue and washout strong CYP3A4 inducers before testing (5.2, 7.2).
- Potential for False Negative Test Results in Recent Onset Hypothalamic Disease:Consider repeat testing if indicated (5.3).

6 ADVERSE REACTIONS to report suspected adverse reactions 1-800-332-1088 to report suspected adverse reactions , contact Aeterna Zentaris GmbH at 1-843-900-2332, or FDA at 1‑800-332-1088 or www.fda.gov/medwatch.

to report suspected adverse reactions
1-800-332-1088

to report suspected adverse reactions , contact Aeterna Zentaris GmbH at 1-843-900-2332, or FDA at 1‑800-332-1088 or www.fda.gov/medwatch.

The most common adverse reactions were dysgeusia, dizziness, headache, fatigue, nausea, hunger, diarrhea, upper respiratory tract infection, feeling hot, hyperhidrosis, nasopharyngitis, and sinus bradycardia (6.1).

FULL PRESCRIBING INFORMATION

1 INDICATIONS AND USAGE

MACRILEN is indicated for the diagnosis of adult growth hormone deficiency (AGHD).

Limitations of Use

The safety and diagnostic performance of MACRILEN have not been established for subjects with a body mass index (BMI) > 40 kg/m^2.

2 DOSAGE AND ADMINISTRATION

2.1 Recommended Dose

The recommended dose is a single oral dose of 0.5 mg/kg of macimorelin. The dose is administered as a reconstituted solution [see Dosage and Administration (2.3)] in patients fasted for at least 8 hours.

2.2 Important Recommendations Before MACRILEN Use

- Discontinue strong CYP3A4 inducers prior to MACRILEN use [see Warning and Precautions (5.2) and Drug Interactions (7.2)].
- Discontinue growth hormone (GH) therapy at least one week before administering MACRILEN [see Drug Interactions (7.3)] .
- Avoid the use of MACRILEN with drugs known to affect pituitary GH secretion [see Drug Interactions (7.3)] .
- For patients with deficiencies in sex hormones, thyroid hormone and/or glucocorticoid, adequately replace each of the missing hormones before administering MACRILEN.
- Ensure that the patient has fasted for at least 8 hours before MACRILEN use.

2.3 Directions for Preparation and Administration

Prepare and administer by a healthcare professional exactly as follows.

Prepare the MACRILEN solution:

1. Weigh the patient in kilograms (i.e., kg).
2. Determine the number of MACRILEN pouches needed to prepare the dose:
3. i. For a patient weighing up to 120 kg, use 1 pouch.
4. ii. For a patient weighing more than 120 kg, use 2 pouches.
5. Use a glass or transparent plastic container with graduation in milliliters (i.e., mL)to dissolve the entire contents of the pouch(es) in the appropriate volume of water.
6. i. For 1 pouch dissolve in 120 mL of water (corresponds to 60 mg/120 mL).
7. ii. For 2 pouches dissolve in 240 mL of water (corresponds to 120 mg/240 mL).
8. Stir the MACRILEN solution gently for about 2 to 3 minutes (a small amount of un-dissolved particles will remain). The solution will have a final concentration of 0.5 mg/mL.
9. Use the MACRILEN solution within 30 minutes after preparation.
10. Discard any unused MACRILEN solution.

Determine the volume of MACRILEN solution needed for the test:

1. Determine the recommended dose to be administered by multiplyingthe patient weight in kilogram by 0.5 mg/kg.
  For example, a 70 kg patient will need a 35 mg dose.
2. Determine the volume of prepared MACRILEN solution to be administered by dividingthe recommended dose by 0.5 mg/mL.
  For example, a patient requiring a dose of 35 mg will need 70 mL of reconstituted MACRILEN solution.
3. Use a syringe (without a needle) with graduations in mL to measure the exact volume of MACRILEN solution to be administered and transfer the required volume of MACRILEN solution into a drinking glass.

Administer the MACRILEN solution and perform the test:

1. Have the patient being tested drink the entire volume of MACRILEN solution in the drinking glass (i.e., the dose) within 30 seconds.
2. Observe the patient being tested per routine for the duration of the test.
3. Draw venous blood samples for GH determination at 30 minutes, 45 minutes, 60 minutes and 90 minutesafter administration of MACRILEN.
4. Prepare serum samples and send to a laboratory for growth hormone determinations.

2.4 Interpretation of MACRILEN Test Results

Clinical studies have established that a maximally stimulated serum GH level of less than 2.8 ng/mL (i.e., at the 30, 45, 60 and 90 minute timepoints) following MACRILEN administration confirms the presence of adult growth hormone deficiency.

3 DOSAGE FORMS AND STRENGTHS

For oral solution: 60 mg white to off-white granules in a pouch for reconstitution in 120 mL of water, resulting in a solution of 0.5 mg/mL of macimorelin.

4 CONTRAINDICATIONS

None

5 WARNINGS AND PRECAUTIONS

5.1 QT Prolongation

MACRILEN causes an increase of about 11 msec in the corrected QT (QTc) interval [see Clinical Pharmacology (12.2)] . QT prolongation can lead to development of torsade de pointes-type ventricular tachycardia with the risk increasing as the degree of prolongation increases. The concomitant use of MACRILEN with drugs that are known to prolong the QT interval should be avoided [see Dosage and Administration (2.2) and Drug Interactions (7.1)] .

5.2 Potential for False Positive Test Results with Use of Strong CYP3A4 Inducers

Concomitant use of strong CYP3A4 inducers with MACRILEN can decrease macimorelin plasma levels significantly and thereby lead to a false positive result [see Drug Interactions (7.2)] . Strong CYP3A4 inducers should be discontinued and enough time should be given to allow washout of CYP3A4 inducers prior to test administration [see Dosage and Administration (2.2)].

5.3 Potential for False Negative Test Results in Recent Onset Hypothalamic Disease

Adult growth hormone (GH) deficiency caused by a hypothalamic lesion may not be detected early in the disease process. Macimorelin acts downstream from the hypothalamus and macimorelin stimulated release of stored GH reserves from the anterior pituitary could produce a false negative result early when the lesion involves the hypothalamus. Repeat testing may be warranted in this situation.

6 ADVERSE REACTIONS to report suspected adverse reactions 1-800-332-1088 to report suspected adverse reactions , contact Aeterna Zentaris GmbH at 1-843-900-2332, or FDA at 1‑800-332-1088 or www.fda.gov/medwatch.

6.1 Clinical Studies Experience to report suspected adverse reactions 1-800-332-1088 to report suspected adverse reactions , contact Aeterna Zentaris GmbH at 1-843-900-2332, or FDA at 1‑800-332-1088 or www.fda.gov/medwatch.

Because clinical trials are conducted under widely varying conditions, adverse reaction rates observed in the clinical trials of a drug cannot be directly compared to rates in the clinical trial of another drug and may not reflect the rates observed in practice.

The data in Table 1are derived from an open-label, randomized, cross-over study that compared the diagnostic performance of MACRILEN to the insulin tolerance test (ITT) for the diagnosis of adult growth hormone deficiency [see Clinical Studies (14)]. A total of 154 subjects with a high to low pre-test probability of having adult growth hormone deficiency received a single oral dose of 0.5 mg/kg MACRILEN. Out of 154 subjects, 58% were male, 42% female, and 86% of white origin. Median values were for age 41 years (range: 18 – 66 years) and body mass index was 27.5 kg/m^2(range: 16 – 40 kg/m^2). Common adverse reactions presented in Table 1were adverse reactions that were not present at baseline and occurred during MACRILEN dosing in at least two individuals.

Table 1: Common Adverse Reactions Reported in at Least Two Individuals Dosed with MACRILEN in an Open-Label Study
 | Number of Subjects (n = 154) | Proportion of Subjects (%)
Dysgeusia | 7 | 4.5
Dizziness | 6 | 3.9
Headache | 6 | 3.9
Fatigue | 6 | 3.9
Nausea | 5 | 3.2
Hunger | 5 | 3.2
Diarrhea | 3 | 1.9
Upper respiratory tract infection | 3 | 1.9
Feeling hot | 2 | 1.3
Hyperhidrosis | 2 | 1.3
Nasopharyngitis | 2 | 1.3
Sinus bradycardia | 2 | 1.3

The safety of Macrilen was evaluated in 126 pediatric patients. The overall safety profile in the pediatric population was consistent with that observed in adults.

7 DRUG INTERACTIONS

7.1 Drugs that Prolong QT Interval

Co-administration of MACRILEN with drugs that prolong the QT interval (such as antipsychotic medications (e.g., chlorpromazine, haloperidol, thioridazine, ziprasidone), antibiotics (e.g., moxifloxacin), Class 1A (e.g., quinidine, procainamide) and Class III (e.g., amiodarone, sotalol) antiarrhythmic medications or any other medications known to prolong the QT interval) may lead to development of torsade de pointes-type ventricular tachycardia. Avoid concomitant use of MACRILEN with drugs that prolong the QT interval. Sufficient washout time of drugs that are known to prolong the QT interval prior to administration of MACRILEN is recommended [see Dosage and Administration (2.2) and Warnings and Precautions (5.1)] .

7.2 Cytochrome P450 (CYP) 3A4 Inducers

Co-administration of a strong CYP3A4 inducer with MACRILEN (e.g., carbamazepine, enzalutamide, mitotane, phenytoin, rifampin, St. John's wort, bosentan, efavirenz, etravirine, modafinil, armodafinil, rufinamide) may reduce the plasma macimorelin concentrations and may lead to false positive test results. Discontinue strong CYP3A4 inducers prior to MACRILEN use. Sufficient washout time of strong CYP3A4 inducers prior to administration of MACRILEN is recommended [see Dosage and Administration (2.2) and Warnings and Precautions (5.2)] .

7.3 Drugs Affecting Growth Hormone Release

The following drugs may impact the accuracy of the MACRILEN diagnostic test. Avoid concomitant use of MACRILEN with the following [see Dosage and Administration (2.2)] :

- Drugs that directly affect the pituitary secretion of growth hormone (such as somatostatin, insulin, glucocorticoids, and cyclooxygenase inhibitors such as aspirin or indomethacin).
- Drugs that may transiently elevate growth hormone concentrations (such as clonidine, levodopa, and insulin).
- Drugs that may blunt the growth hormone response to MACRILEN (such as muscarinic antagonists: atropine, anti-thyroid medication: propylthiouracil, and growth hormone products). Discontinue growth hormone products at least one week before administering the MACRILEN diagnostic test.

Sufficient washout time of drugs affecting growth hormone release prior to administration of MACRILEN is recommended.

8 USE IN SPECIFIC POPULATIONS

8.1 Pregnancy

Risk summary

There are no available data with MACRILEN use in pregnant women to inform a drug associated risk for adverse developmental outcomes. Animal reproduction studies have not been conducted with MACRILEN. MACRILEN is indicated as a single dose which limits the risk of adverse developmental outcomes from exposure to MACRILEN.

The estimated background risk of major birth defects and miscarriage for the indicated populations is unknown. All pregnancies have a background risk of birth defect, loss, or other adverse outcomes. In the U.S. general population, the estimated background risk of major birth defects and miscarriage in clinically recognized pregnancies is 2 – 4% and 15 – 20%, respectively.

8.2 Lactation

Risk Summary

There are no data on the presence of macimorelin in human or animal milk, the effects on the breastfed infant or the effects on milk production. The lack of clinical data during lactation precludes a clear determination of the risk of MACRILEN to an infant during lactation; therefore, the developmental and health benefits of breastfeeding should be considered along with the mother’s clinical need for MACRILEN and any potential adverse effects on the breastfed infant from MACRILEN or the underlying maternal condition.

8.4 Pediatric Use

The safety and efficacy of MACRILEN in pediatric patients have not been established.

The use of MACRILEN for the diagnosis of Growth Hormone Deficiency (GHD) was evaluated in two open-label studies in pediatric patients aged 3 to 17 years of age.

Study 1 (Phase 2) was an open-label, group comparison, dose-escalation single dose escalation study in 24 pediatric patients with suspected GHD. No serious adverse events (SAEs) and no adverse events (AEs) were associated with the macimorelin growth hormone stimulation test (GHST). The study demonstrated a dose-dependent increase in macimorelin exposure and growth hormone (GH) stimulation.

Study 2 (Phase 3) was a multicenter, open-label, randomized, crossover study in 102 pediatric patients with suspected GHD. Patients received a single oral dose of MACRILEN on two different occasions, compared to two standard growth hormone stimulation tests (arginine and clonidine). The primary efficacy endpoint was the area under the receiver operating characteristic (ROC) curve (AUC) assessing the diagnostic accuracy of MACRILEN compared to the adjudicated GHD status. The study failed to meet its primary endpoint; the lower bound of the 97.5% confidence interval for the ROC AUC was 0.66, which did not meet the pre-specified threshold of >0.70.

Diagnostic performance (sensitivity and specificity) was evaluated against a cut-off point of 25.59 ng/mL, which was derived from the study data. Using this cut-off, sensitivity was 78.6% (95% CI: 63.2, 89.7) and specificity was 67.9% (95% CI: 53.7, 80.1). These results did not meet the pre-specified success criteria. An appropriate diagnostic cut-off point could not be established to consistently distinguish between GHD and non-GHD patients in the pediatric population.

8.5 Geriatric Use

Growth hormone secretion normally decreases with age. Therefore, elderly subjects might require a lower cut-off point for diagnosis of adult growth hormone deficiency. Clinical studies of MACRILEN did not include a sufficient number of subjects aged 65 and over to determine whether elderly patients respond differently from younger subjects.

10 OVERDOSAGE

In the event of an overdose, symptomatic and supportive measures should be employed.

11 DESCRIPTION

MACRILEN for oral solution is macimorelin acetate, a synthetic growth hormone secretagogue receptor agonist. Macimorelin acetate is described chemically as D-Tryptophanamide, 2-methylalanyl-N-[(1R)-1-(formylamino)-2-(1H-indol-3-yl)ethyl]-acetate.

The molecular formula for macimorelin acetate is C28H34N6O5with a molecular weight of 534.6 g/mol.

Figure 1: Chemical structure of macimorelin acetate

Each aluminum pouch of MACRILEN contains 60 mg of macimorelin, equivalent to 68 mg of macimorelin acetate, and the following inactive ingredients: lactose monohydrate, crospovidone, sodium stearyl fumarate, saccharin sodium and colloidal silicon dioxide.

12 CLINICAL PHARMACOLOGY

12.1 Mechanism of Action

Macimorelin stimulates GH release by activating growth hormone secretagogue receptors present in the pituitary and hypothalamus.

12.2 Pharmacodynamics

GH stimulation

Maximum GH levels are observed between 30 to 90 minutes after administration of MACRILEN.

Cardiac electrophysiology

The effects of macimorelin on ECG parameters were investigated in a dedicated Thorough QT study that investigated in a 3-way cross-over design with 60 healthy subjects the effects of a supra-therapeutic dose of macimorelin (2 mg/kg) (4 times the recommended dosage) in comparison with placebo and with moxifloxacin. This study showed a mean baseline- and placebo-adjusted change (upper single-sided 95% confidence interval) in QTcF of 9.6 msec (11.4 msec) at 4 h post-dose, which occurred after the mean maximum macimorelin plasma concentration (0.5 h). A similar increase in the QTcF interval was also observed in a single-ascending dose study, which included three dose levels (0.5 mg/kg, and 1 mg/kg and 2 mg/kg (2 times and 4 times the recommended dosage, respectively). All three dose levels studied showed a similar magnitude of QTcF prolongation in the Thorough QT study, suggesting an absence of dose dependent changes. The mechanism for the observed QTcF prolongation is unknown [see Warnings and Precautions (5.1)].

12.3 Pharmacokinetics

The mean plasma macimorelin concentrations are similar between patients with AGHD and healthy subjects for 1.5 hours following administration of a single oral dose of 0.5 mg macimorelin/kg body weight.

Absorption

The maximum plasma macimorelin concentrations (Cmax) were observed between 0.5 hour and 1.5 hours following oral administration of 0.5 mg macimorelin/kg body weight to patients with AGHD under fasting for at least 8 hours. A liquid meal decreased the macimorelin Cmaxand AUC by 55% and 49%, respectively.

Elimination

An in vitrohuman liver microsomes study showed that CYP3A4 is the major enzyme to metabolize macimorelin.

Macimorelin was eliminated with a mean terminal half-life (T1/2) of 4.1 hours following administration of a single oral dose of 0.5 mg macimorelin/kg body weight in healthy subjects.

13 NONCLINICAL TOXICOLOGY

13.1 Carcinogenesis, Mutagenesis, Impairment of Fertility

Carcinogenesis

Long-term carcinogenesis studies in rodents have not been conducted.

Mutagenesis

Macimorelin did not cause mutations in bacteria under assay conditions with or without metabolic activation. There were also no mutations or clastogenic effects in mouse lymphoma cells with or without metabolic activation.

Impairment of Fertility

No studies have been conducted to assess the effect of macimorelin on fertility.

15 CLINICAL STUDIES

The diagnostic efficacy of the MACRILEN test was established in a randomized, open-label, single-dose, cross-over study. The objective of the study was to compare the level of agreement between MACRILEN test results and insulin tolerance test (ITT) results in adult patients with different pre-test probability of growth hormone deficiency and healthy control subjects. The four groups of individuals evaluated were:

- Group A: Adults with a high likelihood of growth hormone deficiency (GHD)
  - Structural hypothalamic or pituitary lesions and low insulin-like growth factor 1 (IGF-1), and/or
  - Three or more pituitary hormone deficiencies and low IGF-1, or
  - Childhood onset GHD with structural lesions and low IGF-1.
- Group B: Adults with an intermediate likelihood of GHD
  - Eligible subjects not qualifying for either high or low likelihood.
- Group C: Adults with a low likelihood of GHD
  - One risk factor for GHD only, such as history of distant traumatic brain injury or one pituitary hormone deficiency only with otherwise normal pituitary function, or
  - Isolated idiopathic childhood onset GHD without additional pituitary deficits.
- Group D: Healthy adult controls
  - Healthy subjects matching Group A subjects by sex, age ± 5 years, body mass index (BMI ± 2 kg/m^2), and estrogen status (females only).

For both the ITT and the MACRILEN test, serum concentrations of growth hormone were measured at 30, 45, 60, and 90 minutes after drug administration. The test was considered positive (i.e., growth hormone deficiency diagnosed) if the maximum serum GH level observed after stimulation was less than the pre-specified cut point value of 2.8 ng/mL for the MACRILEN test or 5.1 ng/mL for the ITT.

The level of negative and positive agreement between the results of the ITT and the MACRILEN test was used to evaluate the performance of the MACRILEN test. In the study, the ITT is used as the benchmark (i.e., a negative ITT indicates absence of disease and a positive ITT indicates presence of disease). Negative agreement is the proportion of subjects with a negative ITT (i.e., those who do not have GHD per the ITT) who also have a negative MACRILEN test. With a high level of negative agreement, the MACRILEN test will not wrongly diagnose an individual without GHD per the ITT as having GHD. Positive agreement is the proportion of subjects with a positive ITT (i.e., those who have GHD per the ITT) who also have a positive MACRILEN test. With a high level of positive agreement, the MACRILEN test will not wrongly diagnose an individual with GHD per the ITT as not having GHD. The agreement measures are defined mathematically below (see Table 2).

Table 2: Definition of Agreement between ITT and MACRILEN
 |  | Insulin Tolerance Test |  | Total
 |  | + | - | Total
MACRILEN | + | a | b | a+b |  | Positive Agreement (%)=100% x a/(a+c)
MACRILEN | - | c | d | c+d |  | Negative Agreement (%)=100% x d/(b+d)
Total |  | a+c | b+d | a+b+c+d |  | Overall Agreement (%)=100% x (a+d)/(a+b+c+d)

Results

One hundred and fifty-seven subjects underwent at least one of the two tests in this study, 59% were male, 41% female, and 86% of white origin. The median age was 41 years (range: 18 – 66 years) and body mass index 27.5 kg/m^2(range: 16 – 40 kg/m^2). The study relied on a cross-over design and each participant was to undergo the two diagnostic tests and serve as his or her own control. Data on both tests were available for 140 subjects; 38 (27%) in Group A, 37 (26%) in Group B, 40 (29%) in Group C, and 25 (18%) in Group D. One out of 154 MACRILEN tests (0.6%) performed failed due to a technical error and 27 out of 157 ITTs (17.2%) performed failed because induction of severe hypoglycemia (i.e., the stimulus) could not be achieved.

Two-by-two tables presenting the pre-specified primary analysis results for the ITT and MACRILEN test are shown below for all subjects (Groups A, B, C, and D combined) and for each group separately (see Table 3). The estimates for negative and positive agreement between MACRILEN and the ITT in the overall study population were 94% and 74% with lower 95% confidence interval bounds 85% and 63%, respectively. Negative and positive agreement between MACRILEN and the ITT in subjects with intermediate or low risk (Groups B and C) were 93% and 61% with lower 95% confidence interval bounds 80% and 43%, respectively. These results are based on peak GH values (maximum GH concentrations across all measurement timepoints).

Table 3: Diagnostic Outcomes for MACRILEN and the ITT in all Subjects (Groups A, B, C, and D) and in Each Group Separately
All Subjects |  | Insulin Tolerance Test |  | Total |  | Agreement Between
All Subjects |  | + | - | Total |  | ITT and MACRILEN
MACRILEN | + | 55 | 4 | 59 |  | Positive | 74%
MACRILEN | - | 19 | 62 | 81 |  | Negative | 94%
Total |  | 74 | 66 | 140 |  | Overall | 84%
Group A High likelihood of AGHD |  | Insulin Tolerance Test |  | Total
Group A High likelihood of AGHD |  | + | - | Total
MACRILEN | + | 33 | 0 | 33 |  | Positive |  | 89%
MACRILEN | - | 4 | 1 | 5 |  | Negative |  | 100%
Total |  | 37 | 1 | 38 |  | Overall |  | 89%
Group B Intermediate likelihood of AGHD |  | Insulin Tolerance Test |  | Total
Group B Intermediate likelihood of AGHD |  | + | - | Total
MACRILEN | + | 20 | 1 | 21 |  | Positive |  | 67%
MACRILEN | - | 10 | 6 | 16 |  | Negative |  | 86%
Total |  | 30 | 7 | 37 |  | Overall |  | 70%
Group C Low likelihood of AGHD |  | Insulin Tolerance Test |  | Total
Group C Low likelihood of AGHD |  | + | - | Total
MACRILEN | + | 2 | 2 | 4 |  | Positive |  | 33%
MACRILEN | - | 4 | 32 | 36 |  | Negative |  | 94%
Total |  | 6 | 34 | 40 |  | Overall |  | 85%
Group D Healthy control |  | Insulin Tolerance Test |  | Total
Group D Healthy control |  | + | - | Total
MACRILEN | + | 0 | 1 | 1 |  | Positive |  | 0%
MACRILEN | - | 1 | 23 | 24 |  | Negative |  | 96%
Total |  | 1 | 24 | 25 |  | Overall |  | 92%

Repeatability was tested in a subset of 34 subjects who underwent two MACRILEN tests. Agreement between the result of the first test and the second test was observed in 31 cases (91.2%).

16 HOW SUPPLIED/STORAGE AND HANDLING

MACRILEN 60 mg is supplied as white to off-white granules in an aluminum pouch. Each pouch contains 60 mg macimorelin (equivalent to 68 mg macimorelin acetate) that when reconstituted with 120 mL of water provides a 60 mg/120 mL (0.5 mg/mL) macimorelin solution.

MACRILEN is available in boxes containing 1 pouch per box (NDC 0169-1401-01).

Before administration, MACRILEN for oral solution must be reconstituted by a healthcare professional [see Dosage and Administration (2.3)].

Store pouches under refrigeration at 2-8°C (36-46°F).

The solution must be used within 30 minutes after preparation. Discard unused portion.

17 PATIENT COUNSELING INFORMATION

Instruct patients to discontinue treatment with GH at least one week before administering MACRILEN. Also, instruct patients to discontinue other medications that may interfere with the diagnostic test results prior to MACRILEN administration [see Drug Interactions (7.2, 7.3)] .

Instruct patients to fast for at least 8 hours before MACRILEN administration [see Dosage and Administration (2.2)].

Manufactured by:
Allphamed Pharbil Arzneimittel GmbH, Goettingen, Germany

Manufactured for: Aeterna Zentaris GmbH, Frankfurt am Main, Germany

MACRILEN™ is a trademark of Aeterna Zentaris GmbH, Frankfurt am Main, Germany

Revised: MM/YYYY

PACKAGE LABEL

NDC 0169-1401-01 List: 140101

Macrilen™

(macimorelin) for oral solution

60 mg

CONTAINS ONE POUCH.

Use the Macrilen™ solution within

30 minutes after preparation.

Discard any unused Macrilen™ solution.

For oral use only.

Rx only